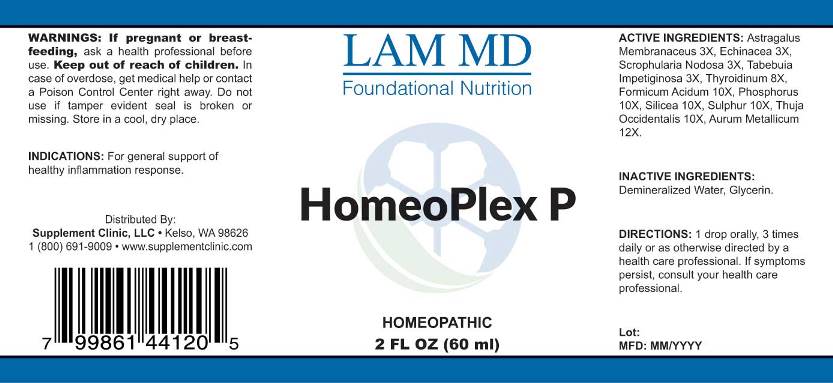 DRUG LABEL: Homeoplex P
NDC: 71781-0007 | Form: LIQUID
Manufacturer: Supplement Clinic, LLC.
Category: homeopathic | Type: HUMAN OTC DRUG LABEL
Date: 20171101

ACTIVE INGREDIENTS: ASTRAGALUS PROPINQUUS ROOT 3 [hp_X]/1 mL; ECHINACEA ANGUSTIFOLIA 3 [hp_X]/1 mL; SCROPHULARIA NODOSA 3 [hp_X]/1 mL; TABEBUIA IMPETIGINOSA BARK 3 [hp_X]/1 mL; SUS SCROFA THYROID 8 [hp_X]/1 mL; FORMIC ACID 10 [hp_X]/1 mL; PHOSPHORUS 10 [hp_X]/1 mL; SILICON DIOXIDE 10 [hp_X]/1 mL; SULFUR 10 [hp_X]/1 mL; THUJA OCCIDENTALIS LEAFY TWIG 10 [hp_X]/1 mL; GOLD 12 [hp_X]/1 mL
INACTIVE INGREDIENTS: WATER; GLYCERIN

Drug Facts:

ACTIVE INGREDIENTS:

Astragalus Membranaceus 3X, Echinacea (Angustifolia) 3X, Scrophularia Nodosa 3X, Tabebuia Impetiginosa 3X, Thyroidinum (Suis) 8X, Formicum Acidum 10X, Phosphorus 10X, Silicea 10X, Sulphur 10X, Thuja Occidentalis 10X, Aurum Metallicum 12X.

INDICATIONS:

For general support of healthy inflammation response.

WARNINGS:

If pregnant or breast-feeding, ask a health professional before use.
Keep out of reach of children. In case of overdose, get medical help or contact a Poison Control Center right away.
Do not use if tamper evident seal is broken or missing.
Store in cool, dry place.

Keep out of reach of children. In case of overdose, get medical help or contact a Poison Control Center right away.

DIRECTIONS:

1 drop orally, 3 times daily or as otherwise directed by a health care professional. If symptoms persist, consult your health care professional.

INDICATIONS:

For general support of healthy inflammation response.

INACTIVE INGREDIENTS:

Demineralized Water, Glycerin

QUESTIONS:

Distributed By:
Supplement Clinic, LLC. • Kelso, WA 98626
1(800)691-9009 • www.supplementclinic.com

PACKAGE LABEL DISPLAY:

LAM MD
Foundational Nutrition

HomeoPlex G

HOMEOPATHIC
2 FL OZ (60 ml)